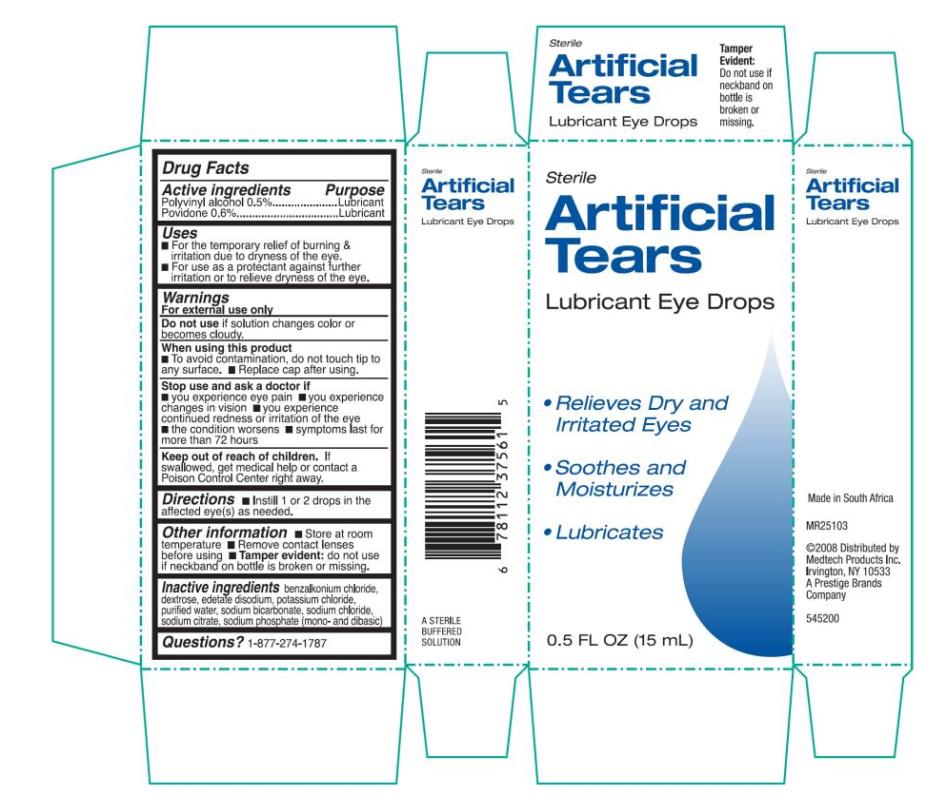 DRUG LABEL: Artificial Tears Lubricant Eye
NDC: 67172-181 | Form: LIQUID
Manufacturer: Prestige Brands Holdings, Inc.
Category: otc | Type: HUMAN OTC DRUG LABEL
Date: 20241025

ACTIVE INGREDIENTS: POLYVINYL ALCOHOL, UNSPECIFIED 5.0 mg/1 mL; POVIDONE 6.0 mg/1 mL
INACTIVE INGREDIENTS: BENZALKONIUM CHLORIDE; DEXTROSE; EDETATE DISODIUM; POTASSIUM CHLORIDE; WATER; SODIUM BICARBONATE; SODIUM CHLORIDE; SODIUM CITRATE; SODIUM PHOSPHATE, DIBASIC; SODIUM PHOSPHATE, MONOBASIC

Artificial Tears Lubricant Eye Drops

Drug Facts

Active ingredients

Polyvinyl alcohol 0.5%

Povidone 0.6%

Purpose

Lubricant

Uses

- For the temporary relief of burning & irritations due to dryness of the eye.
- For use as a protectant against further irritation or to relieve dryness of the eye.

Warnings

For external use only

Do not use if

solution changes color or becomes cloudy.

When using this product:

- to avoid contamination, do not touch tip to any surface.
- replace cap after using.

Stop use and ask a doctor if:

- you experience eye pain
- you experience changes in vision
- you experience continued redness or irritation of the eye
- the condition worsens
- symptoms last for more than 72 hours

Keep out of reach of children.

If swallowed, get medical help or contact a Poison Control Center right away.

Directions

- Instill 1 to 2 drops in the affected eye(s) as needed.

Other information

- Store at room temperature
- Remove contact lenses before using

Inactive ingredients

benzalkonium chloride, dextrose, edetate disodium, potassium chloride, purified water, sodium bicarbonate, sodium chloride, sodium citrate, sodium phosphate (mono- and dibasic)

Questions?

1-877-274-1787

PRINCIPAL DISPLAY PANEL

Sterile
Artificial Tears
Lubricant Eye Drops
0.5 FL OZ (15 mL)